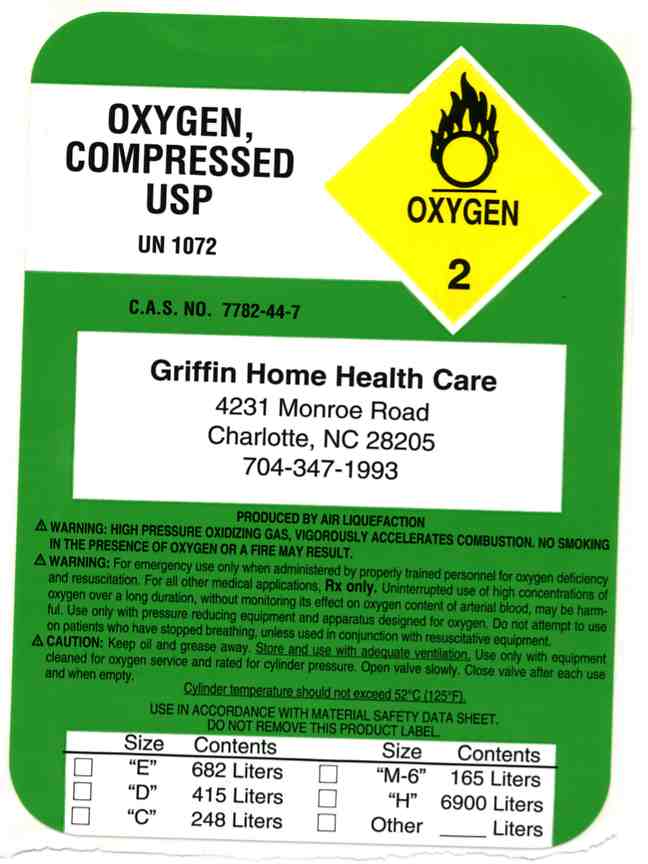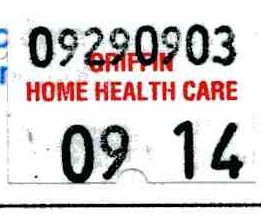 DRUG LABEL: Oxygen
NDC: 66389-0001 | Form: GAS
Manufacturer: Griffin Home Health Care, Inc.
Category: prescription | Type: HUMAN PRESCRIPTION DRUG LABEL
Date: 20091001

ACTIVE INGREDIENTS: Oxygen 99 L/100 L

Oxygen